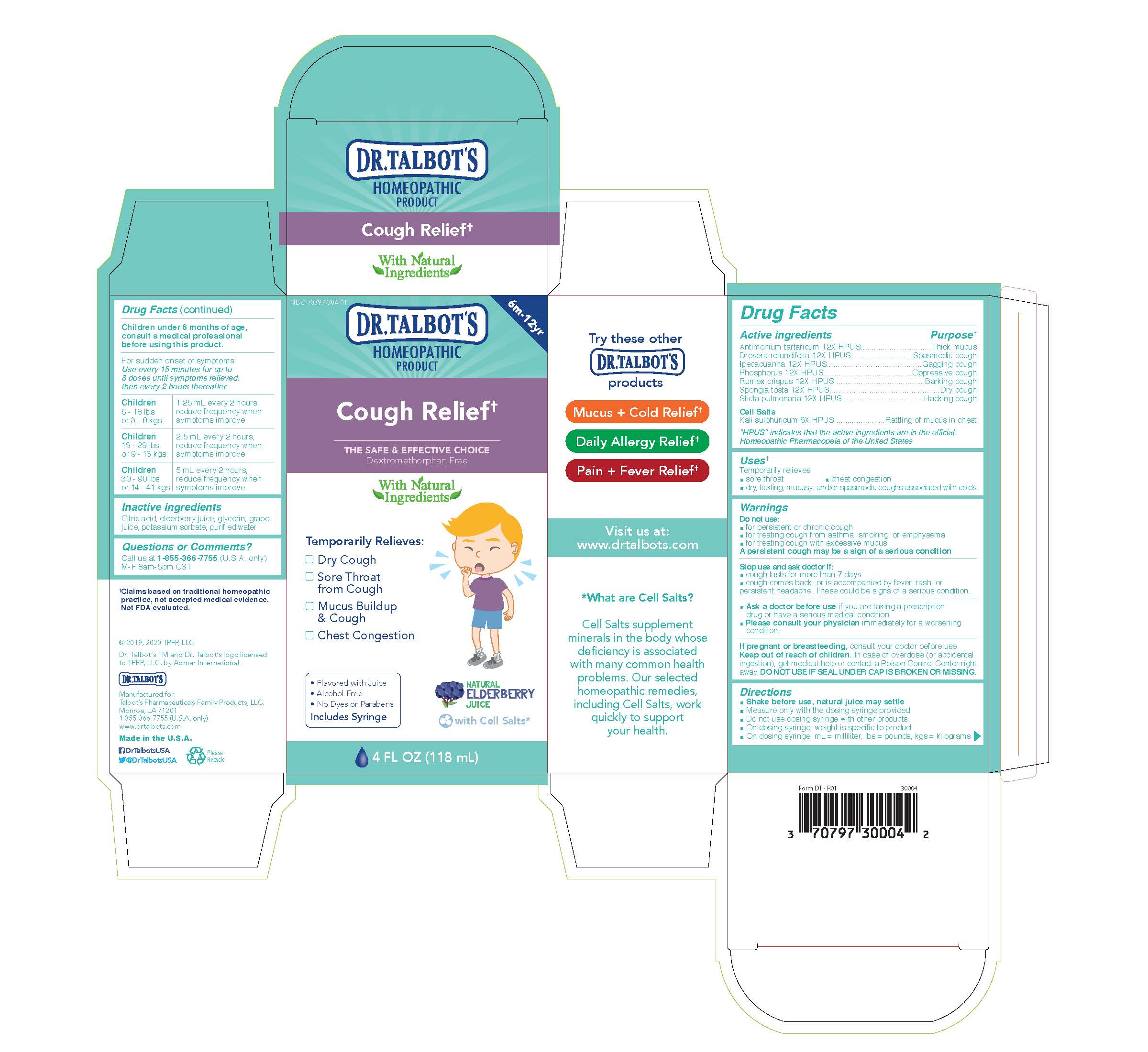 DRUG LABEL: Dr. Talbots Cough Relief
NDC: 70797-314 | Form: LIQUID
Manufacturer: Talbot's Pharmaceuticals Family Products, LLC.
Category: homeopathic | Type: HUMAN OTC DRUG LABEL
Date: 20211005

ACTIVE INGREDIENTS: PULMONARIA OFFICINALIS WHOLE 12 [hp_X]/118 mL; ANTIMONY TARTRATE ION 12 [hp_X]/118 mL; DROSERA ROTUNDIFOLIA FLOWERING TOP 12 [hp_X]/118 mL; PHOSPHORUS 12 [hp_X]/118 mL; RUMEX CRISPUS ROOT 12 [hp_X]/118 mL; POTASSIUM SULFATE 6 [hp_X]/118 mL; SPONGIA OFFICINALIS SKELETON, ROASTED 12 [hp_X]/118 mL; IPECAC 12 [hp_X]/118 mL
INACTIVE INGREDIENTS: EUROPEAN ELDERBERRY JUICE; GLYCERIN; POTASSIUM SORBATE; WATER; CONCORD GRAPE JUICE; CITRIC ACID MONOHYDRATE

Active Ingredients

Antimonium tartaricum 12X HPUS
Drosera rotundifolia 12X HPUS
Ipecacuanha 12X HPUS
Phosphorus 12X HPUS
Rumex crispus 12X HPUS
Spongia Tosta 12X HPUS
Sticta pulmonaria 12X HPUS
Cell Salts
Kali sulphuricum 6X HPUS

Uses

Temporarily relieves

- sore throat
- dry, tickling, mucusy, and/or spasmodic coughs associated with colds
- chest congestion

Warnings

Do not use:

- for persistent or chronic cough
- for treating cough from asthma, smoking, or emphysema
- for treating cough with excessive mucus

A persistent cough may be a sign of a serious condition

Stop use and ask doctor if:

- cough lasts for more than 7 days
- cough comes back, or is accompanied by fever, rash, or persistent headache. These could be signs of a serious condition.
- Ask a doctor before use if you are taking a prescription drug or have a serious medical condition.
- Please consult your physician immediately for a worsening condition.

Pregnancy or breastfeeding

If pregnant or breastfeeding, consult your doctor before use.

Keep out of reach of children. In case of overdoes (or accidental ingestion), get medical help or contact a Poison Control Center right away. DO NOT USE IF SEAL UNDER CAP IS BROKEN OR MISSING.

Directions

- Shake before use, natural juice may settle
- Measure only with the dosing syringe provided
- Do not use dosing syringe with other products
- On dosing syringe, weight is specific to product
- On dosing syringe, ml = milliliter, lbs = pounds, kgs = kilograms

Children under 6 months of age, consult a medical professional before using this product.

For sudden onset of symptoms: Use every 15 minutes for up to 8 doses until symptoms relieved, then every 2 hours thereafter.

Children 6 - 18 lbs or 3 - 8 kgs

1.25 ml every 2 hours, reduce frequency when symptoms improve

Children 19 - 29 lbs or 9 - 13 kgs

2.5 ml every 2 hours, reduce frequency when symptoms improve

Children 30 - 90 lbs or 14 - 41 kgs

5 ml every 2 hours, reduce frequency when symptoms improve

Inactive Ingredients

Citric acid, elderberry juice, glycerin, grape juice, potassium sorbate, purified water

Questions

Questions or Comments?

Call us at 1-800-588-6227

M-F 8am-5pm CST

Purpose

Thick mucus
Spasmodic cough
Gagging cough
Oppresive cough
Barking cough
Dry cough
Hacking cough
Rattling of mucus in chest